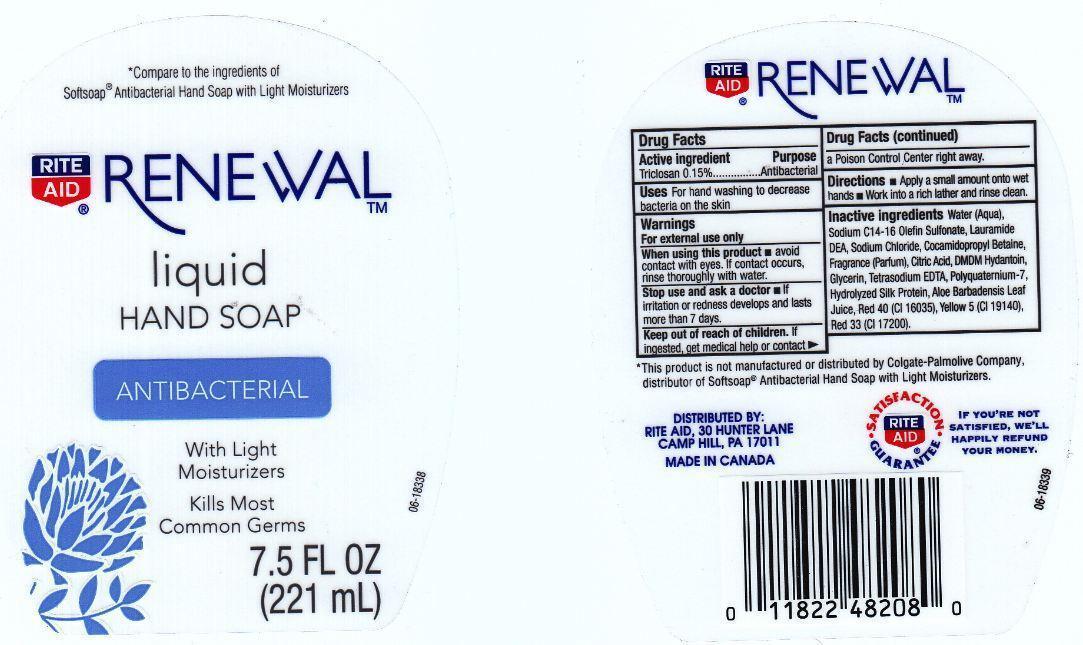 DRUG LABEL: RITE AID RENEWAL
NDC: 11822-2160 | Form: LIQUID
Manufacturer: RITE AID CORPORATION
Category: otc | Type: HUMAN OTC DRUG LABEL
Date: 20121221

ACTIVE INGREDIENTS: TRICLOSAN 1.5 mg/1 mL
INACTIVE INGREDIENTS: WATER; SODIUM C14-16 OLEFIN SULFONATE; LAURIC DIETHANOLAMIDE; SODIUM CHLORIDE; COCAMIDOPROPYL BETAINE; CITRIC ACID MONOHYDRATE; DMDM HYDANTOIN; GLYCERIN; EDETATE SODIUM; POLYQUATERNIUM-7 (70/30 ACRYLAMIDE/DADMAC; 1600000 MW); SILK, BASE HYDROLYZED (1000 MW); ALOE VERA LEAF; FD&C RED NO. 40; FD&C YELLOW NO. 5; D&C RED NO. 33

DRUG FACTS

ACTIVE INGREDIENT

TRICLOSAN 0.15%

PURPOSE

ANTIBACTERIAL

USES

FOR HAND WASHING TO DECREASE BACTERIA ON THE SKIN.

WARNINGS

FOR EXTERNAL USE ONLY.

WHEN USING THIS PRODUCT

AVOID CONTACT WITH EYES. IF CONTACT OCCURS, RINSE THOROUGHLY WITH WATER.

STOP USE AND ASK A DOCTOR

IF IRRITATION OR REDNESS DEVELOPS AND LASTS MORE THAN 7 DAYS.

KEEP OUT OF REACH OF CHILDREN

IF INGESTED, GET MEDICAL HELP OR CONTACT A POISON CONTROL CENTER RIGHT AWAY.

DIRECTIONS

APPLY A SMALL AMOUNT ONTO WET HANDS. WORK INTO A RICH LATHER AND RINSE CLEAN.

INACTIVE INGREDIENTS

WATER (AQUA), SODIUM C14-16 OLEFIN SULFONATE, LAURAMIDE DEA, SODIUM CHLORIDE, COCAMIDOPROPYL BETAINE, FRAGRANCE (PARFUM), CITRIC ACID, DMDM HYDANTOIN, GLYCERIN, TETRASODIUM EDTA, POLYQUATERNIUM-7, HYDROLYZED SILK PROTEIN, ALOE BARBADENSIS LEAF JUICE, RED 40 (CI 16035), YELLOW 5 (CI 19140), RED 33 (CI 17200).